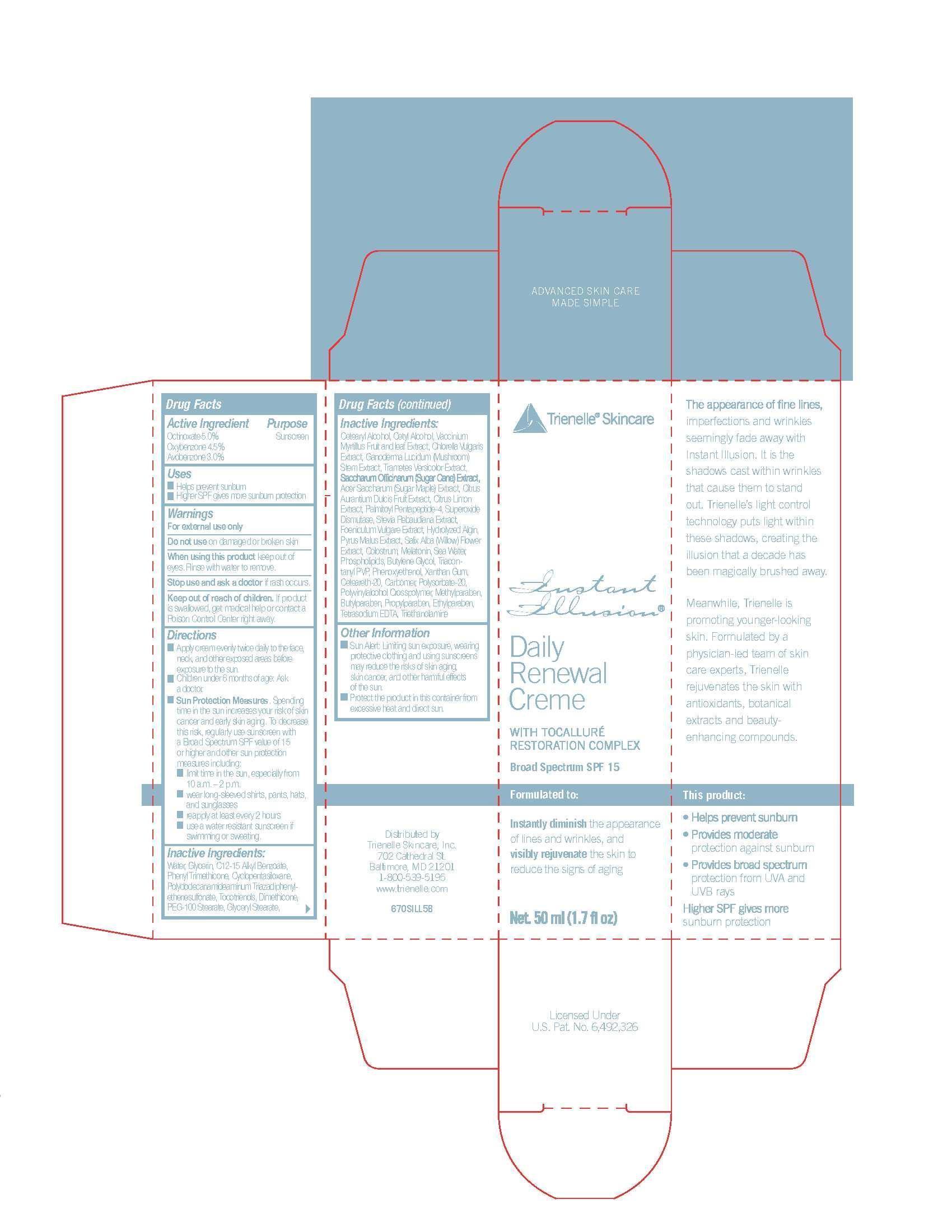 DRUG LABEL: Trienelle Skincare Instant Illusion Daily Renewal Creme
NDC: 50972-455 | Form: CREAM
Manufacturer: NewMarket Health Products LLC
Category: otc | Type: HUMAN OTC DRUG LABEL
Date: 20140930

ACTIVE INGREDIENTS: OCTINOXATE 5 mg/1 g; OXYBENZONE 4.5 mg/1 g; AVOBENZONE 3 mg/1 g
INACTIVE INGREDIENTS: WATER; GLYCERIN; C12-15 ALKYL BENZOATE; PHENYL TRIMETHICONE; CYCLOMETHICONE 5; POLYVINYL ALCOHOL; TOCOTRIENOLS; DIMETHICONE; PEG-100 STEARATE; GLYCERYL MONOSTEARATE; CETOSTEARYL ALCOHOL; CETYL ALCOHOL; VACCINIUM MYRTILLUS FRUITING TOP; VACCINIUM MYRTILLUS LEAF; CHLORELLA VULGARIS; GANODERMA LUCIDUM STEM; TRAMETES VERSICOLOR FRUITING BODY; SUGARCANE; ACER SACCHARUM WHOLE; ORANGE; LEMON; PALMITOYL PENTAPEPTIDE-4; SUPEROXIDE DISMUTASE (CU-ZN) SACCHAROMYCES CEREVISIAE; STEVIA REBAUDIUNA LEAF; FOENICULUM VULGARE WHOLE; LAMINARIA DIGITATA HYDROLYZED ALGINIC ACID; APPLE; SALIX ALBA FLOWER; BOS TAURUS COLOSTRUM; MELATONIN; SODIUM CHLORIDE; GLYCINE MAX WHOLE; BUTYLENE GLYCOL; TRIACONTANYL PVP (WP-660); PHENOXYETHANOL; XANTHAN GUM; POLYOXYL 20 CETOSTEARYL ETHER; CARBOMER 940; POLYSORBATE 20; NYLON-12; BLANCOPHOR R; METHYLPARABEN; BUTYLPARABEN; PROPYLPARABEN; ETHYLPARABEN; EDETATE SODIUM; TROLAMINE

Trienelle Skincare Instant Illusion Daily Renewal Creme

Drugs Facts

Active Ingredient

Octinoxate 5.0%

Oxybenzone 4.5%

Avobenzone 3.0%

Purpose

Sunscreen

Uses

- Helps prevent sunburn
- Higher SPF gives more sunburn protection

Warnings

For external use only

Do not use on damaged or broken skin

When using this product keep out of eyes. Rinse with water to remove.

Stop use and ask a doctor if rash occurs.

KEEP OUT OF REACH OF CHILDREN

Keep out of reachof children. If product is swallowed, get medical help or contact a Poison Control Center right away.

Directions

- Apply cream evenly twice daily to face, neck, and other exposed areas before exposure to the sun.
- Children under 6 months of age: Ask a doctor.
- Sun Protection Measures. Spending time in the sun increases your risk of skin cancer and early skin aging. To decrease this risk, regularly use sunscreen with a Broad Spectrum SPF value of 15 or higher and other sun protection measures including:
- limit time in the sun, especially from 10 a.m. - 2 p.m.
- wear long-sleeved shirts, pants, hats, and sunglasses
- reapply at least every 2 hours
- use a water resistant sunscreen if swimming or sweating.

INACTIVE INGREDIENT

Water, Glycerin, C12-15 Alkyl Benzoate, Phenyl Trimethicone, Cyclopentasiloxane, Polydodecanamideaminum Triadiphenylethenesulfonate, Tocotrienols, Dimethicone, PEG-100 Stearate, Glyceryl Stearate, Cetearyl Alcohol, Cetyl Alcohol, Vaccinium Myrtillus Fruit and Leaf Extract, Chlorella Vulgaris Extract, Ganoderma Lucidum (Mushroom) Stem Extract, Trametes Versicolor Extract, Saccharum Officinarum (Sugar Cane) Extract, Acer Saccharum (Sugar Maple) Extract, Citrus Aurantium Dulcis Fruit Extract, Citrus Limon Extract, Palmitoyl Pentapeptide-4, Superoxide Dismutase, Stevia Rebaudiana Extract, Foeniculum Vulgare Extract, Hydrolyzed Algin, Pryus Malus Extract, Salix Alba (Willow) Flower Extract, Colostrum, Melatonin, Sea Water, Phospholipids, Butylene Glycol, Triacontanyl PVP, Phenoxyethenol, Xanthan Gum, Ceteareth-20, Carbomer, Polysorbate-20, Polyvinylalcohol Crosspolymer, Methylparaben, Butylparaben, Propylparaben, Ethylparaben, Tetrasodium EDTA, Triethanolamine

Other Information

- Sun Alert: Limiting sun exposure, wearing, protective clothing and using sunscreens may reduce the risks of skin aging, skin cancer, and other harmful effects of the sun.
- Protect the product in this container from excessive heat and direct sun.

QUESTIONS

Distributed by

Trienelle Skincare, Inc.

702 Cathedral St.

Baltimore, MD 21201

1-800-539-5195

www.trienelle.com

PACKAGE LABEL

Trienelle Skincare

Instant Illusion

Daily Renewal Creme

WITH TOCALLURÉ RESTORATION COMPLEX

Broad Spectrum SPF 15

Formulated to: Instantly diminish the appearance of lines and wrinkles, and visibly rejuvenate the skin to reduce the signs of aging

Net. 50 ml (1.7 fl oz)